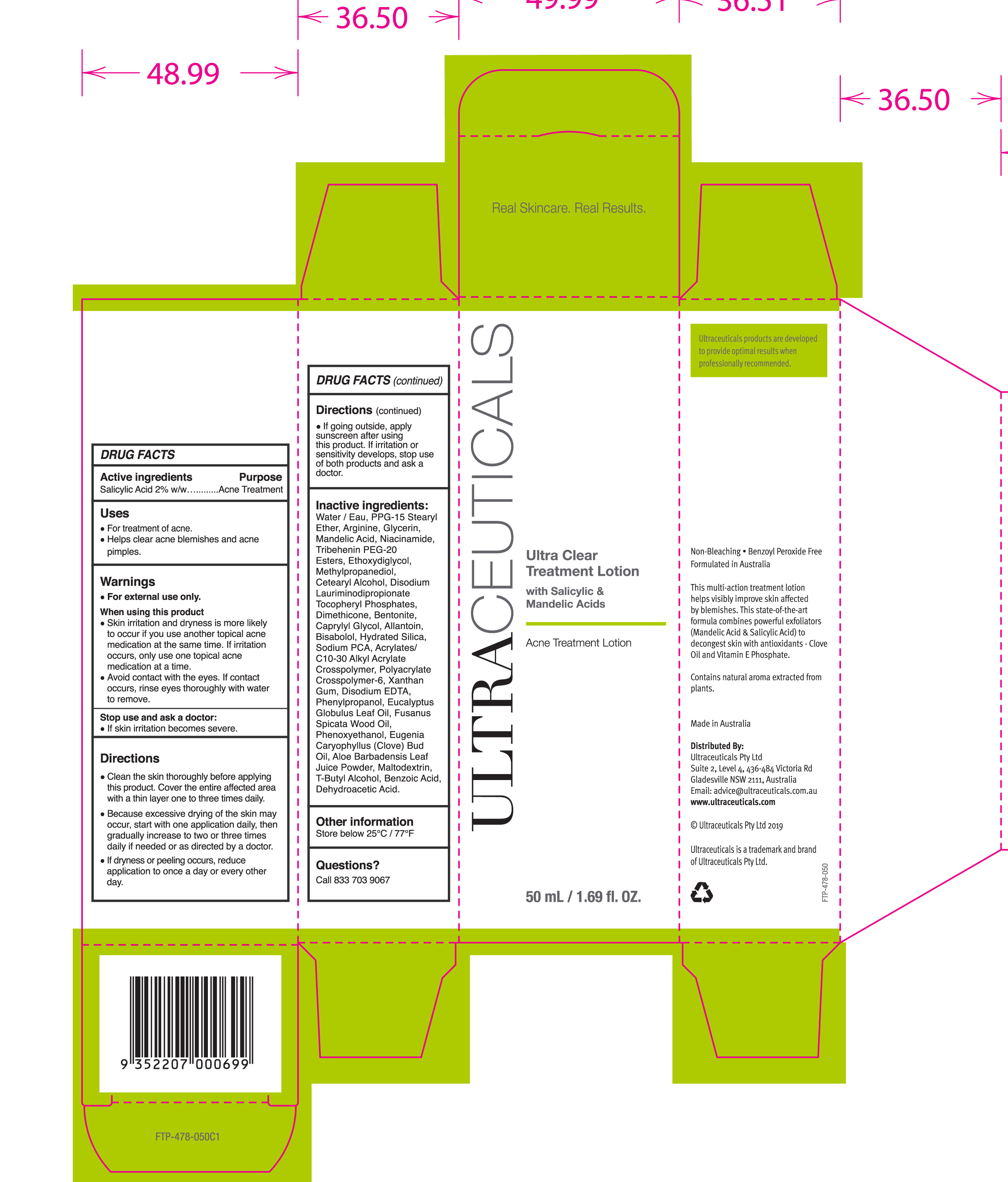 DRUG LABEL: Ultra Clear Treatment
NDC: 10028-051 | Form: LOTION
Manufacturer: ULTRACEUTICALS PTY LIMITED
Category: otc | Type: HUMAN OTC DRUG LABEL
Date: 20251007

ACTIVE INGREDIENTS: SALICYLIC ACID 2 g/100 mL
INACTIVE INGREDIENTS: LEVOMENOL; HYDRATED SILICA; XANTHAN GUM; DISODIUM LAURIMINODIPROPIONATE TOCOPHERYL PHOSPHATES; BENTONITE; SANTALUM SPICATUM OIL; WATER; CLOVE OIL; ALOE VERA LEAF; TERT-BUTYL ALCOHOL; BENZOIC ACID; DEHYDROACETIC ACID; PPG-15 STEARYL ETHER; ARGININE; GLYCERIN; NIACINAMIDE; TRIBEHENIN PEG-20 ESTERS; ALLANTOIN; PHENOXYETHANOL; MALTODEXTRIN; METHYLPROPANEDIOL; CETOSTEARYL ALCOHOL; DIMETHICONE; CAPRYLYL GLYCOL; AMMONIUM ACRYLOYLDIMETHYLTAURATE, DIMETHYLACRYLAMIDE, LAURYL METHACRYLATE AND LAURETH-4 METHACRYLATE COPOLYMER, TRIMETHYLOLPROPANE TRIACRYLATE CROSSLINKED (45000 MPA.S); EDETATE DISODIUM; PHENYLPROPANOL; MANDELIC ACID; DIETHYLENE GLYCOL MONOETHYL ETHER; SODIUM PYRROLIDONE CARBOXYLATE; EUCALYPTUS OIL

Ultra Clear Treatment Lotion
with salicylic and mandelic acid

Active ingredients Purpose

Salicylic Acid 2% w/w Acne Treatment

Uses

For treatment of acne
Helps clear acne blemishes and acne pimples

Stop use and ask a doctor:

If skin irritation becomes severe.

When using this product

Skin irritation and dryness is more likely to occur if you use another topical acne medication at the same time. If irritation occurs, only use one topical acne medication at a time.
Avoid contact with the eyes. If contact occurs, rinse eyes thoroughly with water to remove.

Warnings

For external use only.

When using this product

Skin irritation and dryness is more likely to occur if you use another topical acne medication at the same time. If irritation occurs, only use one topical acne medication at a time.
Avoid contact with the eyes. If contact occurs, rinse eyes thoroughly with water to remove.

Directions

- Clean the skin thoroughly before applying this product. Cover the entire affected area with a thin layer one to three times daily.
- Because excessive drying of the skin may occur, start with one application daily, then gradually increase to two or three times daily if needed or as directed by a doctor.
- If dryness or peeling occurs, reduce application to once a day or every other day.
- If going outside, apply sunscreen after using this product. If irritation or sensitivity develops, stop use of both products and ask a doctor.

Inactive ingredients

Water/Eau, PPG-15 Stearyl Ether, Arginine, Glycerin, Mandelic Acid, Niacinamide, Tribehenin PEG-20 Esters, Ethoxydiglycol, Methylpropanediol, Cetearyl Alcohol, Disodium Laurimodipropionate Tocopheryl Phosphates, Dimethicone, Bentonite, Caprylyl Glycol, Allantoin, Bisabolol, Hydrated Silica, Sodium PCA, Acrylates/C10-30 Alkyl Acrylate Crosspolymer, Polyacrylate Crosspolymer-6 Xanthan Gum, Disodium EDTA, Phenylpropanol, Eucalyptus Globulus Leaf Oil, Fusanus Spicata Wood Oil, Phenoxyethanol, Eugenia Caryophyllus (Clove) Bud Oil, Aloe Barbadensis Leaf Juice Powder, Maltodextrin, T-Butyl Alcohol, Benzoic Acid, Dehydroacetic Acid.

PACKAGE LABEL

Ultraceuticals

Ultra Clear Treatment Lotion

with Salicylic & Mandelic Acid

Acne Treatment Lotion

50mL / 1.69 fl OZ